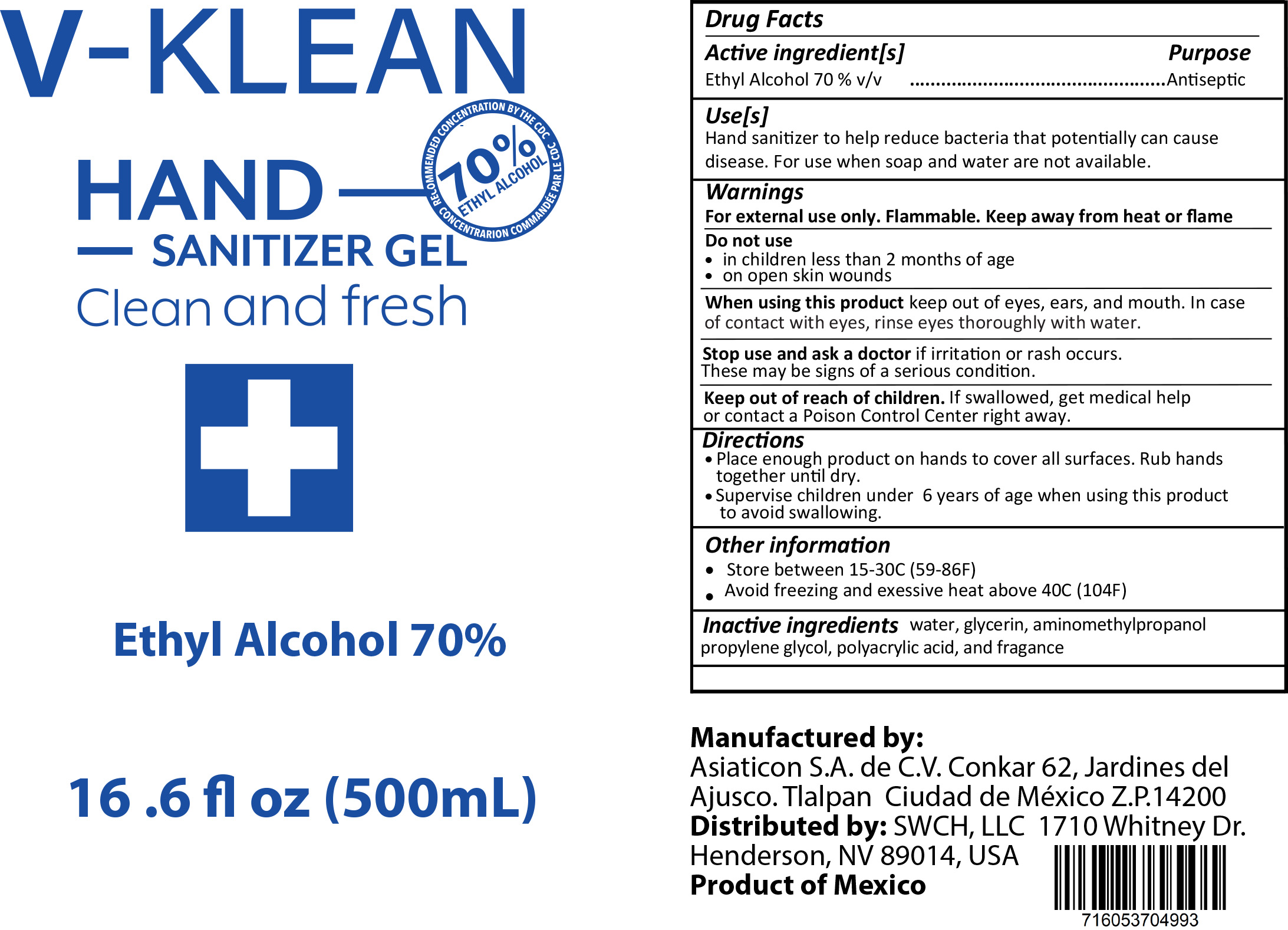 DRUG LABEL: V-KLEAN
NDC: 75192-100 | Form: GEL
Manufacturer: Asiaticon, S.A. de C.V.
Category: otc | Type: HUMAN OTC DRUG LABEL
Date: 20200428

ACTIVE INGREDIENTS: ALCOHOL 70 mL/100 mL
INACTIVE INGREDIENTS: AMINOMETHYLPROPANOL 0.5 mL/100 mL; WATER 27.85 mL/100 mL; GLYCERIN 0.85 mL/100 mL; FRAGRANCE LAVENDER & CHIA F-153480 0.2 mL/100 mL; PROPYLENE GLYCOL 0.3 mL/100 mL; POLYACRYLIC ACID (8000 MW) 0.3 mL/100 mL

Directions

Place enough product on hands to cover all surfaces. Rub hands together until dry.

Supervise children under 6 years of age when using this product to avoid swallowing.

Warnings

Flammable, keep away from fire and flames

For external use only

Inactive ingredients

water, glycerin, aminomethylpropanol, propylene glycol, polyacrylic acid, and fragrance

Use

Hand sanitizer for hand-washing to decrease bacteria on the skin, only when water is not available

Keep out of reach of children. If swallowed, get medical help or contact a Poison Control Center right away.

Purpose

Antiseptic, Hand sanitizer

Active Ingredient(s)

Ethyl alcohol 70%

PACKAGE LABEL

500 mL NDC: 75192-100-01